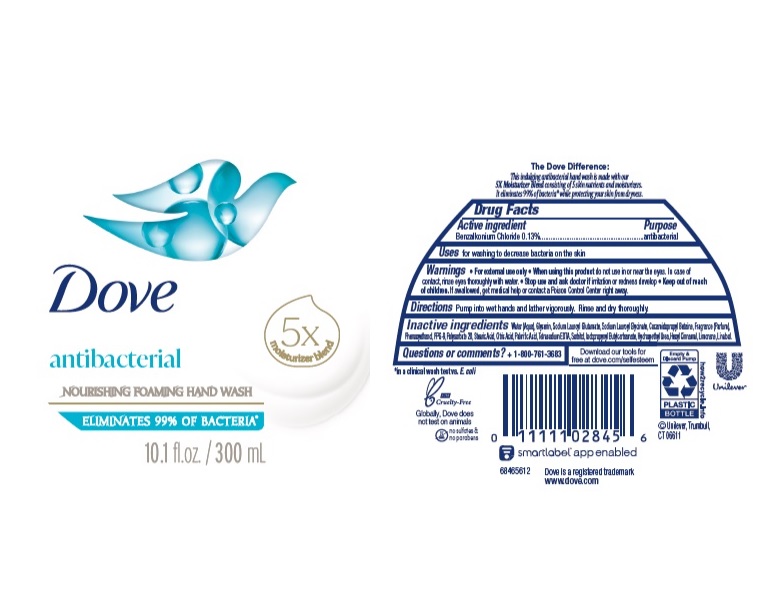 DRUG LABEL: Dove
NDC: 64942-1848 | Form: LIQUID
Manufacturer: Conopco Inc. d/b/a/ Unilever
Category: otc | Type: HUMAN OTC DRUG LABEL
Date: 20241107

ACTIVE INGREDIENTS: BENZALKONIUM CHLORIDE 1.3 mg/1 mL
INACTIVE INGREDIENTS: SODIUM LAUROYL GLUTAMATE; STEARIC ACID; PPG-9; CITRIC ACID MONOHYDRATE; WATER; GLYCERIN; COCAMIDOPROPYL BETAINE; PALMITIC ACID; EDETATE SODIUM; SODIUM LAUROYL GLYCINATE; POLYSORBATE 20; SORBITOL; PHENOXYETHANOL; HYDROXYETHYL UREA; .ALPHA.-HEXYLCINNAMALDEHYDE; IODOPROPYNYL BUTYLCARBAMATE; LIMONENE, (+)-; LINALOOL, (+/-)-

Dove Care & Protect Antibacterial Nourishing Foaming Hand Wash

DOVE CARE & PROTECT ANTIBACTERIAL NOURISHING FOAMING HAND WASH - Benzalkonium Chloride

Dove Care & Protect Antibacterial Nourishing Foaming Hand Wash

Drug Facts

Active ingredient

Benzalkonium Chloride 0.13%

Purpose

Antibacterial

Uses

For washing to decrease bacteria on the skin

Warnings

• For external use only
• When using this product do not use in or near the eyes. In case of contact, rinse eyes thoroughly with wate r
• Stop use and ask doctor if irritation or redness develop.

• Keep out of reach of children except under adult supervision.

If swallowed, get medical help or contact a poison control Center right away.

Directions

Pump into wet hands and lather vigorously. Rinse and dry thoroughly.

Inactive ingredients

Water (Aqua), Sodium Lauroyl Glutamate, Sodium Lauroyl Glycinate, Cocamidopropyl Betaine, Fragrance (Parfum), Phenoxyethanol, PPG-9, Polysorbate 20, Stearic Acid, Citric Acid, Palmitic Acid, Tetrasodium EDTA, Sorbitol, Iodopropynyl Butylcarbamate, Hydroxyethyl Urea, Hexyl Cinnamal, Limonene, Linalool.

Questions or Comments?

1-800-761-3683